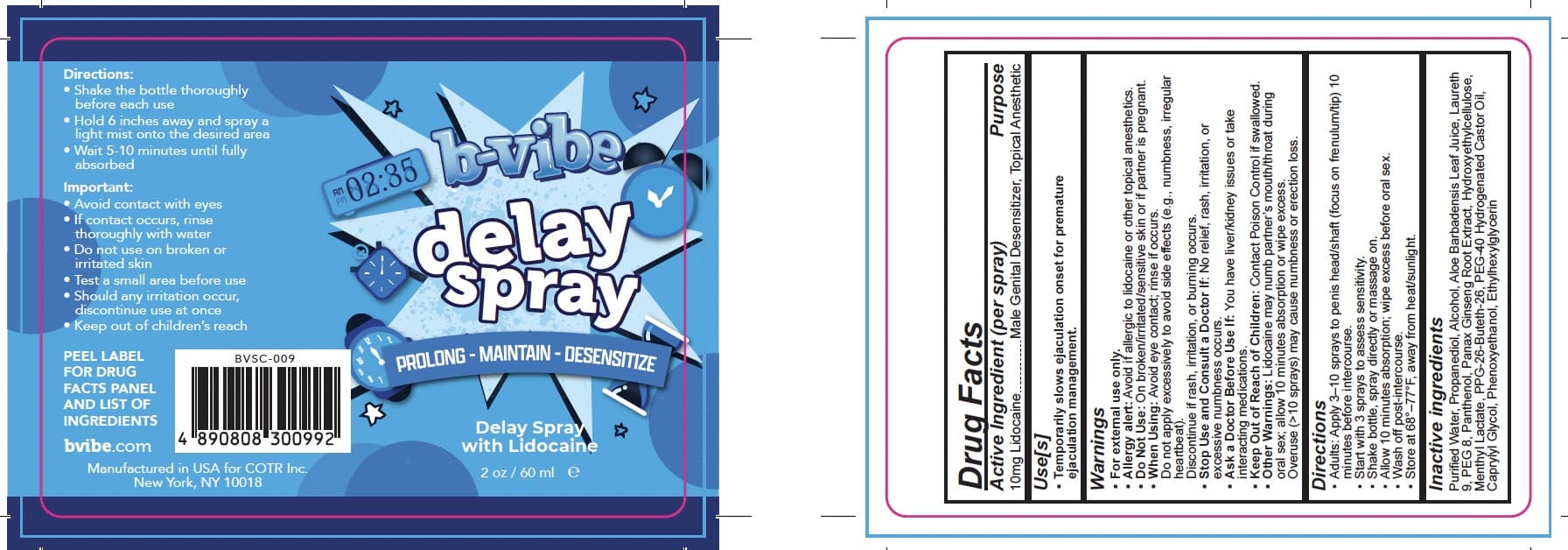 DRUG LABEL: BVibe
NDC: 85775-111 | Form: LIQUID
Manufacturer: COTR Inc
Category: otc | Type: HUMAN OTC DRUG LABEL
Date: 20250712

ACTIVE INGREDIENTS: LIDOCAINE HYDROCHLORIDE 9.94 mg/0.1 mL
INACTIVE INGREDIENTS: ALOE BARBADENSIS LEAF JUICE; WATER; HYDROXYETHYLCELLULOSE; METHYL LACTATE; DECETH-7; PROPANEDIOL; ASIAN GINSENG; PANTOTHENIC ACID; PHENOXYETHANOL; ALCOHOL; CAPRYLYL GLYCOL; ETHYLHEXYLGLYCERIN; PEG-8

COTR-PLP Delay Spray

Active Ingredient(s)

Lidocaine HCl 9.94 mg

Purpose

Male Genital Desensitizer Topical Anesthetic

Use

Temporarily slows ejaculation onset for premature ejaculation management.

Warnings

For external use only.
Allergy alert: Avoid if allergic to lidocaine or other topical anesthetics.
Do Not Use: On broken/irritated/sensitive skin or if partner is pregnant.
When Using: Avoid eye contact; rinse if occurs.
Do not apply excessively to avoid side effects (e.g., numbness, irregular heartbeat).
Discontinue if rash, irritation, or burning occurs.
Stop Use and Consult a Doctor If: No relief, rash, irritation, or excessive numbness occurs.
Ask a Doctor Before Use If: You have liver/kidney issues or take interacting medications.
Keep Out of Reach of Children: Contact Poison Control if swallowed.
Other Warnings: Lidocaine may numb partner's mouth/throat during oral sex; allow 10 minutes absorption or wipe excess.
Overuse (>10 sprays) may cause numbness or erection loss.

KEEP OUT OF REACH OF CHILDREN

Keep out of reach of childeren.Contact Poison Control if

Directions

Adults: Apply 3-10 sprays to penis head/shaft (focus on frenulum/tip) 10 minutes before intercourse.
Start with 3 sprays to assess sensitivity.
Shake bottle, spray directly or massage on.
Allow 10 minutes absorption; wipe excess before oral sex.
Wash off post-intercourse.

Store at 68°-77°F, away from heat/sunlight.

Inactive ingredients

Purified Water, Propanediol, Alcohol, Aloe Barbadensis Leaf Juice, Laureth 9, PEG 8, Panthenol, Panax Ginseng Root Extract, Hydroxyethy|cellulose, Menthyl Lactate, PPG-26-Buteth-26, PEG-40 Hydrogenated Castor Oil, Caprylyl Glycol, Phenoxyethanol, Ethylhexylglycerin